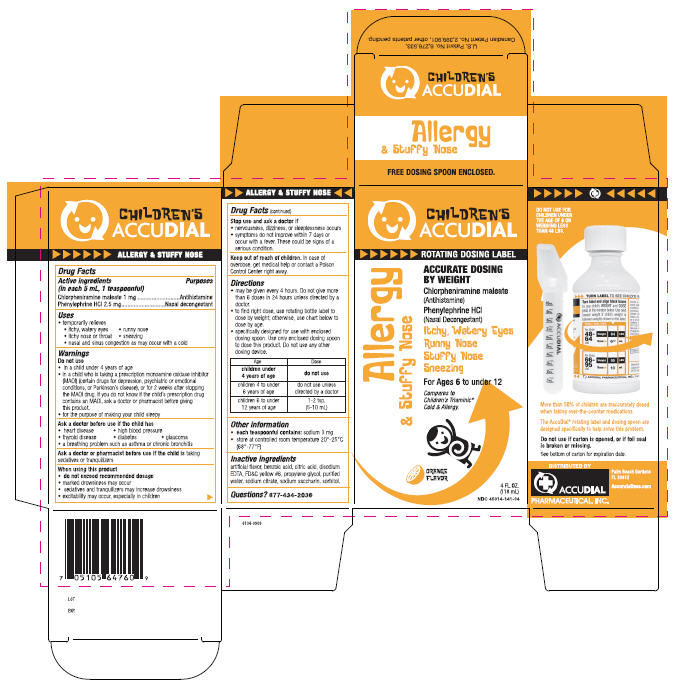 DRUG LABEL: Allergy and Stuffy Nose
NDC: 45014-141 | Form: LIQUID
Manufacturer: Accudial Pharmaceutical, Inc.
Category: otc | Type: HUMAN OTC DRUG LABEL
Date: 20091111

ACTIVE INGREDIENTS: Chlorpheniramine Maleate 1 mg/5 mL; Phenylephrine Hydrochloride 2.5 mg/5 mL
INACTIVE INGREDIENTS: Orange; Benzoic Acid; Citric Acid Monohydrate; Edetate Disodium; FD&C YELLOW NO. 6; Propylene Glycol; Water; Sodium Citrate; Saccharin Sodium; Sorbitol

Children's
ACCUDIAL

ALLERGY & STUFFY NOSE

Drug Facts

ACTIVE INGREDIENT

PURPOSE

Active ingredients (in each 5 mL, 1 teaspoonful) | Purposes
Chlorpheniramine maleate 1 mg | Antihistamine
Phenylephrine HCl 2.5 mg | Nasal decongestant

Uses

- temporarily relieves
  - itchy, watery eyes
  - runny nose
  - itchy nose or throat
  - sneezing
  - nasal and sinus congestion as may occur with a cold

Warnings

Do not use

- in a child under 4 years of age
- in a child who is taking a prescription monoamine oxidase inhibitor (MAOI) (certain drugs for depression, psychiatric or emotional conditions, or Parkinson's disease), or for 2 weeks after stopping the MAOI drug. If you do not know if the child's prescription drug contains an MAOI, ask a doctor or pharmacist before giving this product.
- for the purpose of making your child sleepy

Ask a doctor before use if the child has

- heart disease
- high blood pressure
- thyroid disease
- diabetes
- glaucoma
- a breathing problem such as asthma or chronic bronchitis

Ask a doctor or pharmacist before use if the child is taking sedatives or tranquilizers

When using this product

- do not exceed recommended dosage
- marked drowsiness may occur
- sedatives and tranquilizers may increase drowsiness
- excitability may occur, especially in children

Stop use and ask a doctor if

- nervousness, dizziness, or sleeplessness occurs
- symptoms do not improve within 7 days or occur with a fever. These could be signs of a serious condition.

Keep out of reach of children. In case of overdose, get medical help or contact a Poison Control Center right away.

Directions

- may be given every 4 hours. Do not give more than 6 doses in 24 hours unless directed by a doctor.
- to find right dose, use rotating bottle label to dose by weight; otherwise, use chart below to dose by age.
- specifically designed for use with enclosed dosing spoon. Use only enclosed dosing spoon to dose this product. Do not use any other dosing device.

Age | Dose
children under 4 years of age | do not use
children 4 to under 6 years of age | do not use unless directed by a doctor
children 6 to under 12 years of age | 1-2 tsp. (5-10 mL)

Other information

- each teaspoonful contains: sodium 3 mg
- store at controlled room temperature 20°-25°C (68°-77°F)

Inactive ingredients

artificial flavor, benzoic acid, citric acid, disodium EDTA, FD&C yellow #6, propylene glycol, purified water, sodium citrate, sodium saccharin, sorbitol.

Questions?

877-434-2036

PRINCIPAL DISPLAY PANEL - 118 mL Carton

CHILDREN'S
ACCUDIAL

ROTATING DOSING LABEL

Allergy
& Stuffy Nose

ACCURATE DOSING
BY WEIGHT

Chlorpheniramine maleate
(Antihistamine)

Phenylephrine HCl
(Nasal Decongestant)

Itchy, Watery Eyes
Runny Nose
Stuffy Nose
Sneezing

For Ages 6 to under 12

Compares to
Children's Triaminic®
Cold & Allergy.

ORANGE
FLAVOR

4 FL. OZ.
(118 mL)
NDC 45014-141-04